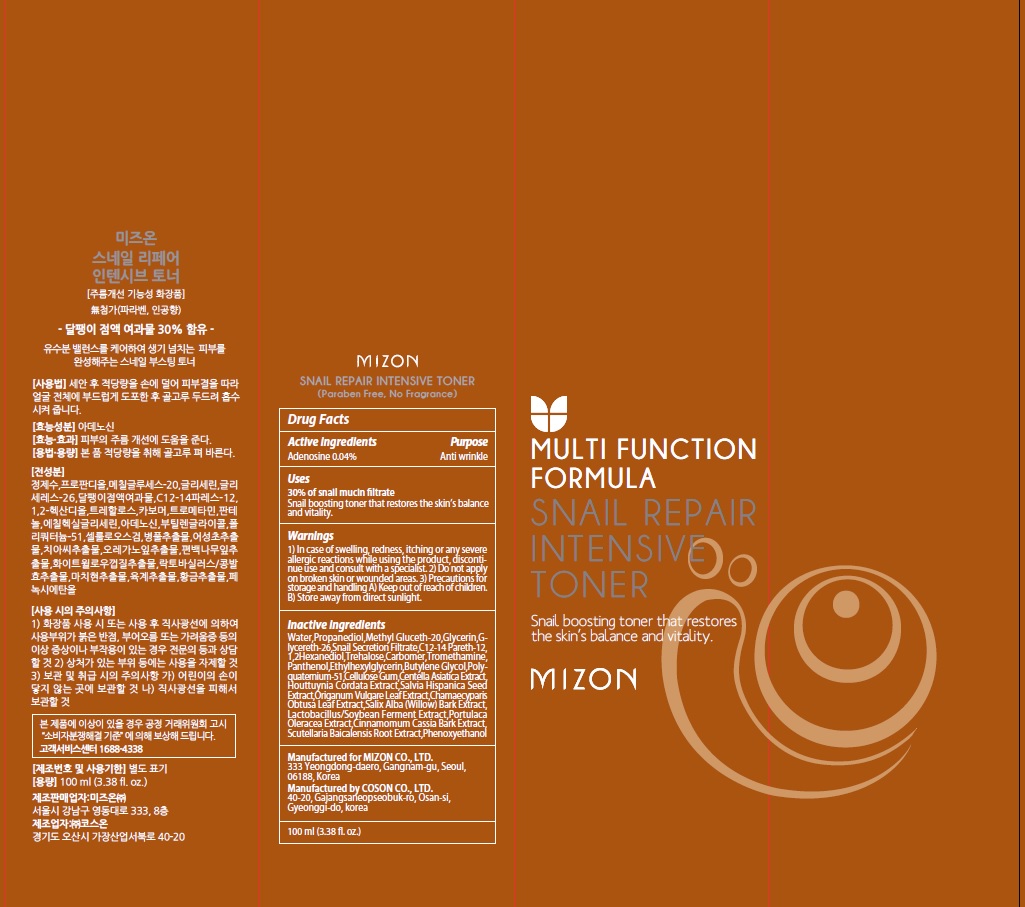 DRUG LABEL: MIZON SNAIL REPAIR INTENSIVE TONER
NDC: 57718-220 | Form: LIQUID
Manufacturer: MIZON CO.,LTD.
Category: otc | Type: HUMAN OTC DRUG LABEL
Date: 20180719

ACTIVE INGREDIENTS: Adenosine 0.04 g/100 mL
INACTIVE INGREDIENTS: Water; Propanediol

ACTIVE INGREDIENT

Active ingredients: Adenosine 0.04%

INACTIVE INGREDIENT

Inactive ingredients:

Water,Propanediol,Methyl Gluceth-20,Glycerin,Glycereth-26,Snail Secretion Filtrate,C12-14 Pareth-12, 1,2Hexanediol,Trehalose,Carbomer,Tromethamine,Panthenol,Ethylhexylglycerin,Butylene Glycol,Polyquaternium-51, Cellulose Gum,Centella Asiatica Extract,Houttuynia Cordata Extract,Salvia Hispanica Seed Extract,Origanum Vulgare Leaf Extract,Chamaecyparis Obtusa Leaf Extract,Salix Alba (Willow) Bark Extract,Lactobacillus/Soybean Ferment Extract,Portulaca Oleracea Extract,Cinnamomum Cassia Bark Extract,Scutellaria Baicalensis Root Extract,Phenoxyethanol

PURPOSE

Purpose: Anti wrinkle

WARNINGS

1) In case of swelling, redness, itching or any severe allergic reactions while using the product, discontinue use and consult with a specialist. 2) Do not apply on broken skin or wounded areas. 3) Precautions for storage and handling A) Keep out of reach of children. B) Store away from direct sunlight.

KEEP OUT OF REACH OF CHILDREN

Uses

30% of snail mucin filtrate

Snail boosting toner that restores the skin’s balance and vitality.

Directions

After cleansing, use a cotton soaked with the toner and swipe the liquid over your face twice daily, morning and evening. Follow with Collagen Power Lifting emulsion and cream